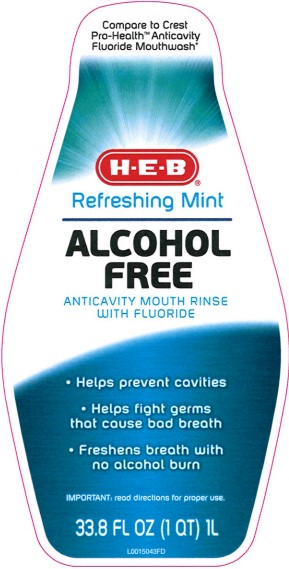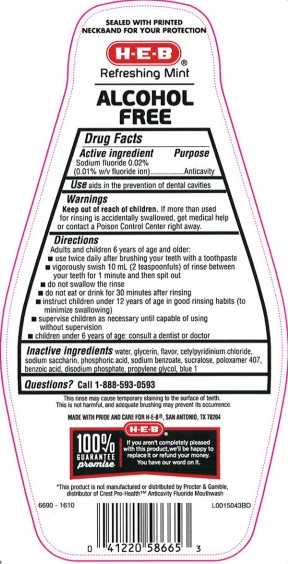 DRUG LABEL: Alcohol Free Refreshing Mint
NDC: 37808-576 | Form: MOUTHWASH
Manufacturer: H E B
Category: otc | Type: HUMAN OTC DRUG LABEL
Date: 20260224

ACTIVE INGREDIENTS: SODIUM FLUORIDE 0.1 mg/1 mL
INACTIVE INGREDIENTS: WATER; GLYCERIN; CETYLPYRIDINIUM CHLORIDE; SACCHARIN SODIUM; PHOSPHORIC ACID; SODIUM BENZOATE; SUCRALOSE; POLOXAMER 407; BENZOIC ACID; SODIUM PHOSPHATE, DIBASIC, ANHYDROUS; PROPYLENE GLYCOL; FD&C BLUE NO. 1

HEB 576.001/576AC-AD
Alcohol Free Fluoride Refreshing Mint Mouthwash

TEP

SEALED WITH PRINTED NECKBAND FOR YOUR PROTECTION

claims

H-E-B

Refreshing Mint

ALCOHOL

FREE

Active ingredient

Sodium fluoride 0.02% (0.01% w/v fluoride ion)

Purpose

Anticavity

Use

aids in the prevention of dental cavities

Warnings

For this product

Keep out of reach of children.

If more than used for rinsing is accidentally swallowed, get medical help or contact a Poison Control Center right away.

Directions

Adults and children 6 years of age and oler:

- use twice a day after brushing your teeth with toothpaste.
- vigorously swish 10 mL (2 teaspoonfuls) of rinse between your teeth for 1 minute and then spit out
- do not swallow the rinse
- do not eat or drink for 30 minutes after rinsing
- instruct children under 12 years of age in good rinsing habits (to minimize swallowing)
- supervise children as necessary until capable of using without supervision
- children under 6 years of age: consult a dentist or doctor

Inactive ingredients

water, glycerin, flavor, cetylpyridinium chloride, sodium saccharin, phosphoric acid, sodium benzoate, sucralose, poloxamer 407, benzoic acid, disodium phosphate, propylene glycol, blue 1

Questions?

Call 1-888-593-0593

Claims

This rinse may cause temporary staining to the surface of teeth.

This is not harmful, and adequate brushing may prevent its occurrence.

Adverse Reactions

MADE WITH PRIDE AND CARE FOR H-E-B, SAN ANTONIO, TX 78204

HEB 100% GUARANTEE promise

If you aren't completely pleased with this product, we'll be happy to replace it or refund your money. You have our word on it.

Disclaimer

*This product is not manufactured or distributed by Procter & Gamble, distributor of Crest Pro-Health Anticavity Fluoride Mouthwash

principal display panel

Compare to Crest Pro-Health™ Anticavity Fluoride MouthWash*

H-E-B®

Refreshing Mint

ALCOHOL

FREE

ANTICAVITY MOUTH RINSE

WITH FLUORIDE

- Helps prevent cavities
- Helps fight germs that cause bad breath
- Freshens breath with no alcohol burn

IMPORTANT: read directions for proper use.

33.8 FL OZ (1 QT) 1L